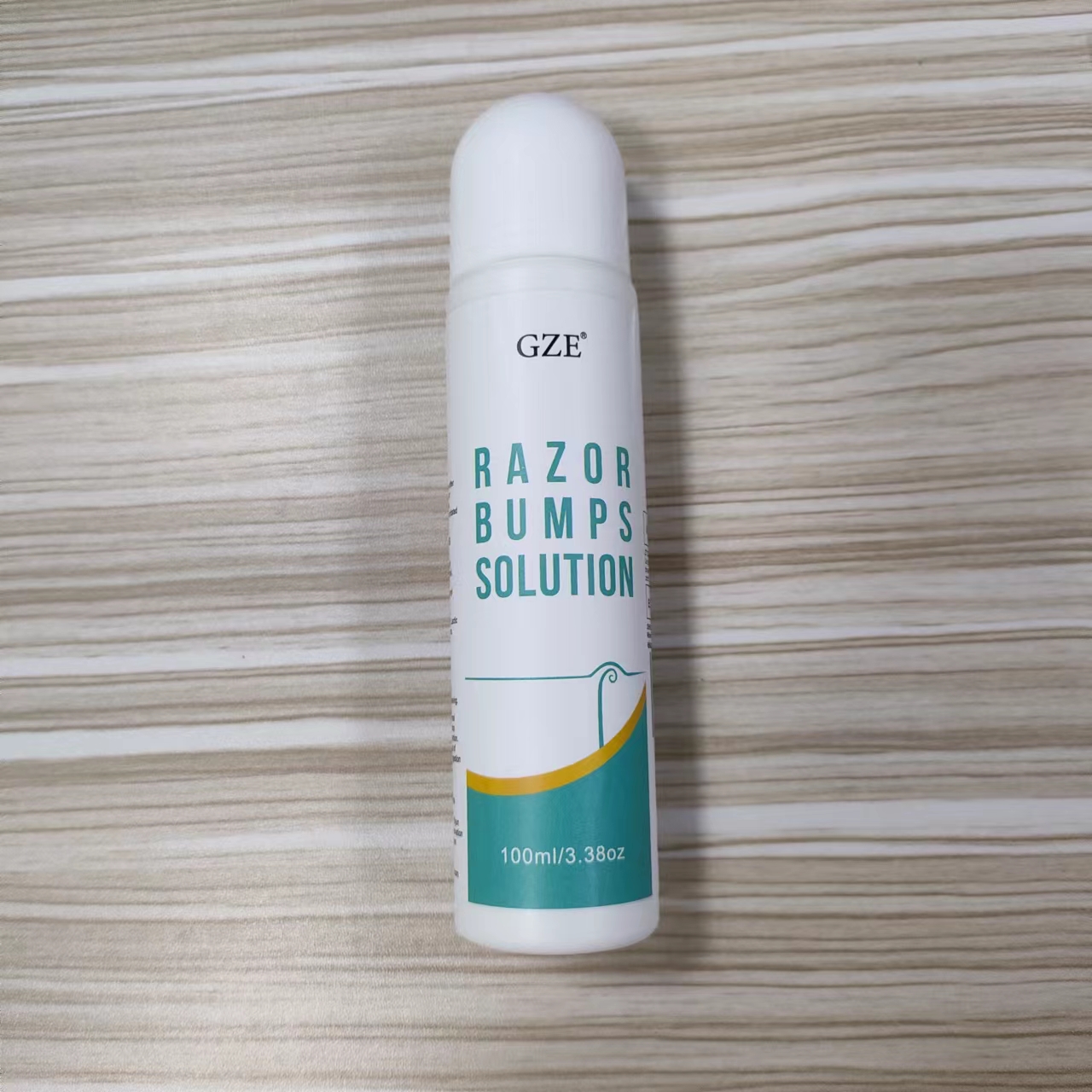 DRUG LABEL: GZE Razor Bumps Solution
NDC: 74458-208 | Form: LOTION
Manufacturer: Guangzhou Yilong Cosmetics Co., Ltd
Category: otc | Type: HUMAN OTC DRUG LABEL
Date: 20241011

ACTIVE INGREDIENTS: TETRAHYDRODIFERULOYLMETHANE 1 g/100 mL; SALICYLIC ACID 1 g/100 mL; CAMPHOR (NATURAL) 0.5 g/100 mL; ASPIRIN 5 g/100 mL; DIMETHYLMETHOXY CHROMANYL PALMITATE 0.1 g/100 mL
INACTIVE INGREDIENTS: PHENOXYETHANOL; WATER; PROPYLENE GLYCOL; ISOPROPYL ALCOHOL; GLYCERIN; GLYCOLIC ACID; CYCLOMETHICONE 6; HYDROXYETHYL CELLULOSE, UNSPECIFIED; LACTIC ACID; TOCOPHEROL; BUTYLENE GLYCOL

GZE RAZOR BUMPS SOLUTION

ACTIVE INGREDIENT

Dimethylmethoxy Chromanyl Palmitate 0.1%

Tetrahydrodiferuloylmethane 1%

Camphor 0.5%

Salicylic Acid 1%

Acetyl Salicylic Acid 5%

INACTIVE INGREDIENT

Aqua

Isopropyl Alcohol

Glycerin

Butylene Glycol

Propylene Glycol

Glycolic Acid

Lactic Acid

Camphor

Tocopherol

Cyclohexasiloxane

Hydroxyethylcellulose

Phenoxyethanol

PURPOSE

Calms redness after shaving.

INDICATIONS AND USAGE

Use daily after waxing or shaving.

WARNINGS

For external use only.

Stop use and ask a doctor if rash occurs.

Do not use on damaged or broken skin.

When using this product keep out of eyes. Rinse with water to remove.

Keep out of reach of children. If swallowed, get medical help or contact a Poison Control Center right away.

DOSAGE AND ADMINISTRATION

Use daily after waxing and shaving.